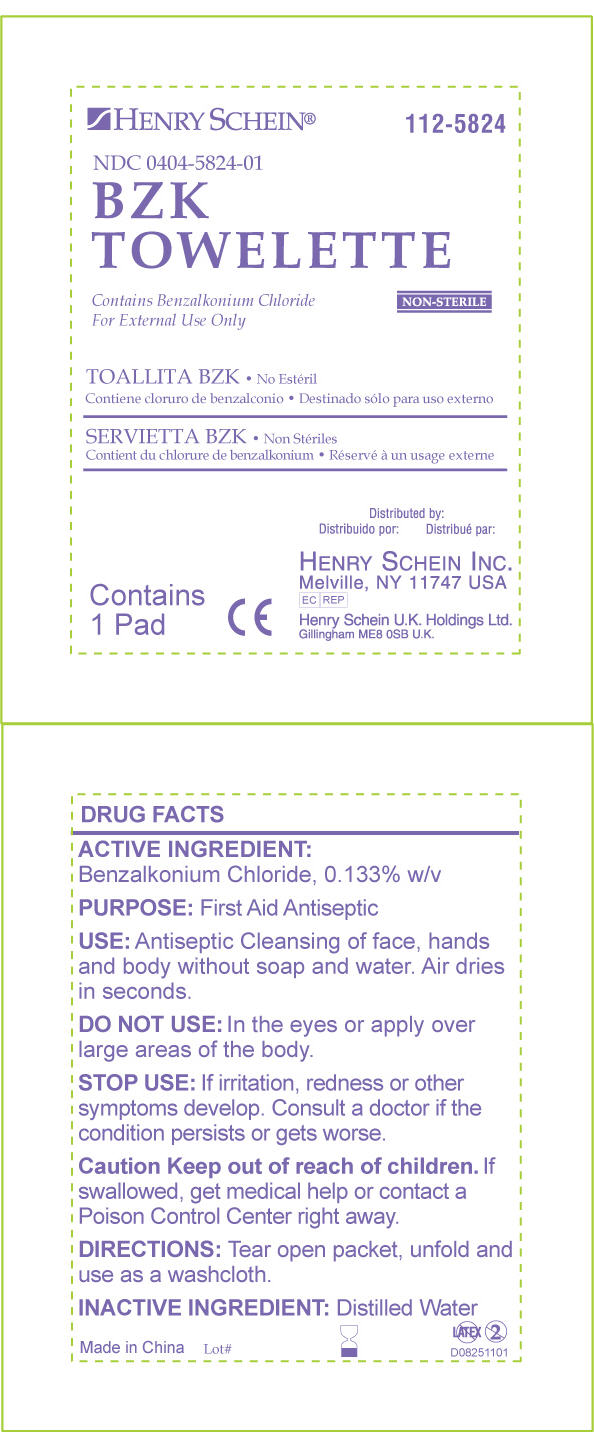 DRUG LABEL: BZK Towelette
NDC: 0404-5824 | Form: SWAB
Manufacturer: Henry Schein Inc.
Category: otc | Type: HUMAN OTC DRUG LABEL
Date: 20111005

ACTIVE INGREDIENTS: BENZALKONIUM CHLORIDE 0.001 mL/1.4 mL
INACTIVE INGREDIENTS: WATER

Drug Facts

ACTIVE INGREDIENT:

Benzalkonium Chloride, 0.133% w/v

PURPOSE:

First Aid Antiseptic

KEEP OUT OF REACH OF CHILDREN

Caution Keep out of reach of children. If swallowed, get medical help or contact a Poison Control Center right away.

INDICATIONS AND USAGE

USE: Antiseptic Cleansing of face, hands and body without soap and water. Air dries in seconds.

DO NOT USE: In the eyes or apply over large areas of the body.

STOP USE: If irritation, redness or other symptoms develop. Consult a doctor if the condition persists or gets worse.

DOSAGE AND ADMINISTRATION

Contains 1 Pad

DIRECTIONS: Tear open packet, unfold and use as washcloth

INACTIVE INGREDIENT: Distilled Water

PRINCIPAL DISPLAY PANEL - Pouch Label

HENRY SCHEIN®
112-5824

NDC 0404-5824-01

BZK
TOWELETTE

Contains Benzalkonium Chloride
For External Use Only
NON-STERILE

Contains
1 Pad

CE

Distributed by:

HENRY SCHEIN INC.
Melville, NY 11747 USA
EC REP

Henry Schein U.K. Holdings Ltd.
Gillingham ME8 0SB U.K.